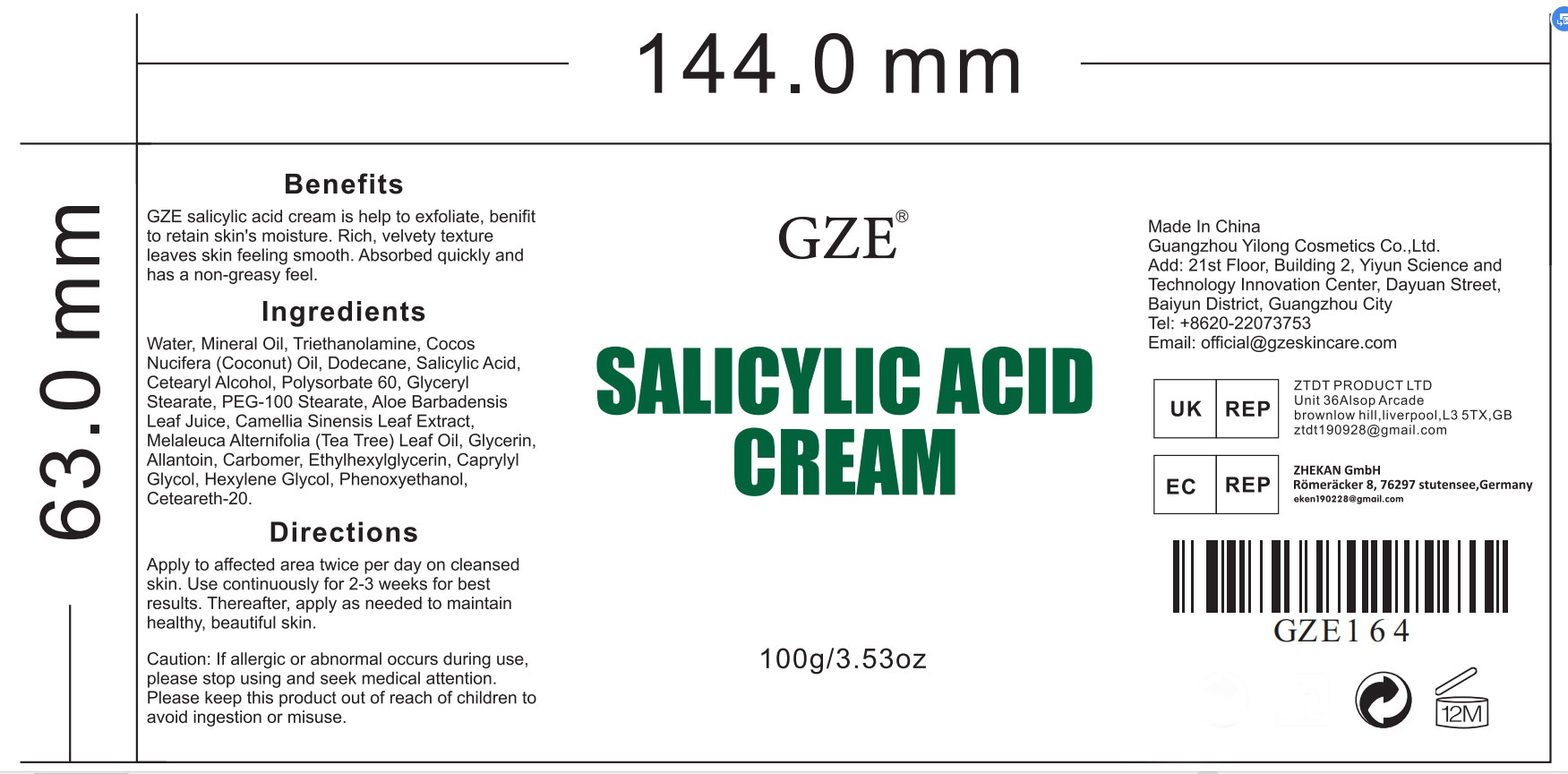 DRUG LABEL: GZE Salicylic Acid Cream
NDC: 74458-164 | Form: CREAM
Manufacturer: Guangzhou Yilong Cosmetics Co., Ltd
Category: otc | Type: HUMAN OTC DRUG LABEL
Date: 20241015

ACTIVE INGREDIENTS: ALLANTOIN 4 g/100 g; SALICYLIC ACID 2 g/100 g
INACTIVE INGREDIENTS: GLYCERIN; ETHYLHEXYLGLYCERIN; WATER; TROLAMINE; POLYSORBATE 60; GLYCERYL MONOSTEARATE; HEXYLENE GLYCOL; PHENOXYETHANOL; ALOE VERA LEAF; COCONUT OIL; GREEN TEA LEAF; PEG-100 STEARATE; TEA TREE OIL; MINERAL OIL; POLYOXYL 20 CETOSTEARYL ETHER; CETOSTEARYL ALCOHOL; DODECANE; CARBOMER HOMOPOLYMER, UNSPECIFIED TYPE; CAPRYLYL GLYCOL

GZE SALICYLIC ACID CREAM

ACTIVE INGREDIENT

Salicylic Acid 2%

Allantoin 4%

INACTIVE INGREDIENT

Aqua

Mineral Oil

Triethanolamine

Cocos Nucifera (Coconut) Oil

Dodecane

Cetearyl Alcohol

Polysorbate 60

Glyceryl Stearate

PEG-100 Stearate

Aloe Barbadensis Leaf Juice

Camellia Sinensis Leaf Extract

Melaleuca Alternifolia (Tea Tree) Leaf Oil

Glycerin

Carbomer

Ethylhexylglycerin

Caprylyl Glycol

Hexylene Glycol

Phenoxyethanol

Ceteareth-20

PURPOSE

Exfoliates and brightens skin tone

INDICATIONS AND USAGE

Apply to affected area twice per day on cleansed skin. Use continuously for 2-3 weeks for best results. Thereafter, apply as needed to maintain healthy, beautiful skin.

WARNINGS

For external use only.

Stop use and ask a doctor if rash occurs.

Do not use on damaged or broken skin.

When using this product keep out of eyes. Rinse with water to remove.

Keep out of reach of children. If swallowed, get medical help or contact a Poison Control Center right away.

DOSAGE AND ADMINISTRATION

Apply to affected area twice per day on cleansed skin. Use continuously for 2-3 weeks for best results. Thereafter, apply as needed to maintain healthy, beautiful skin.